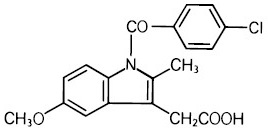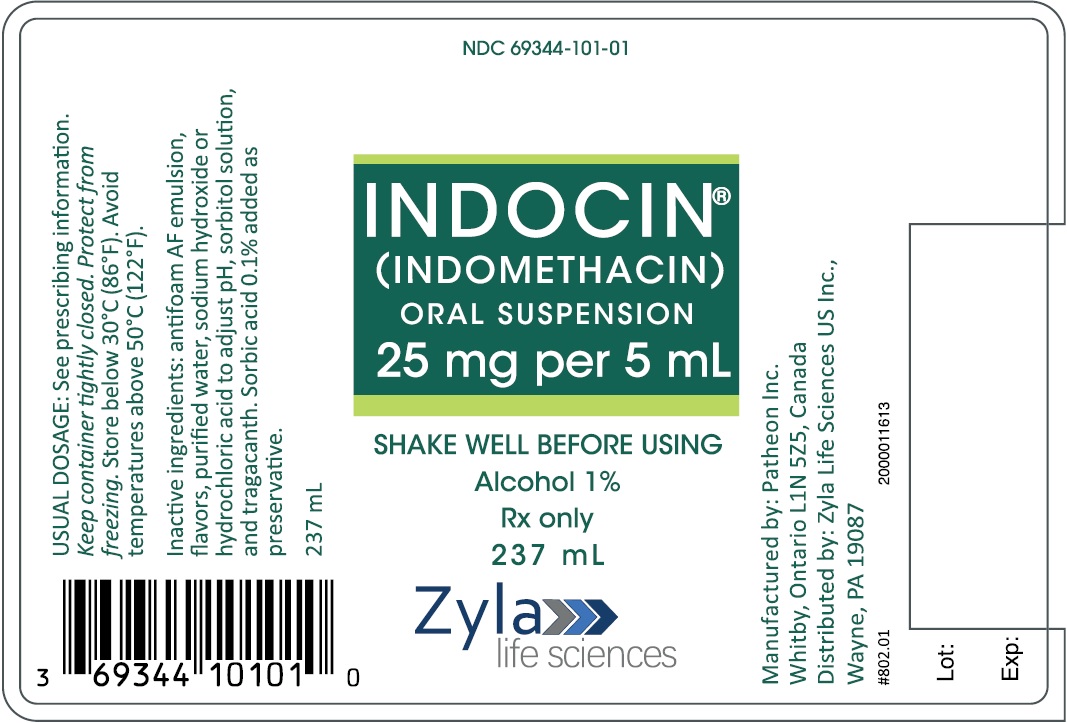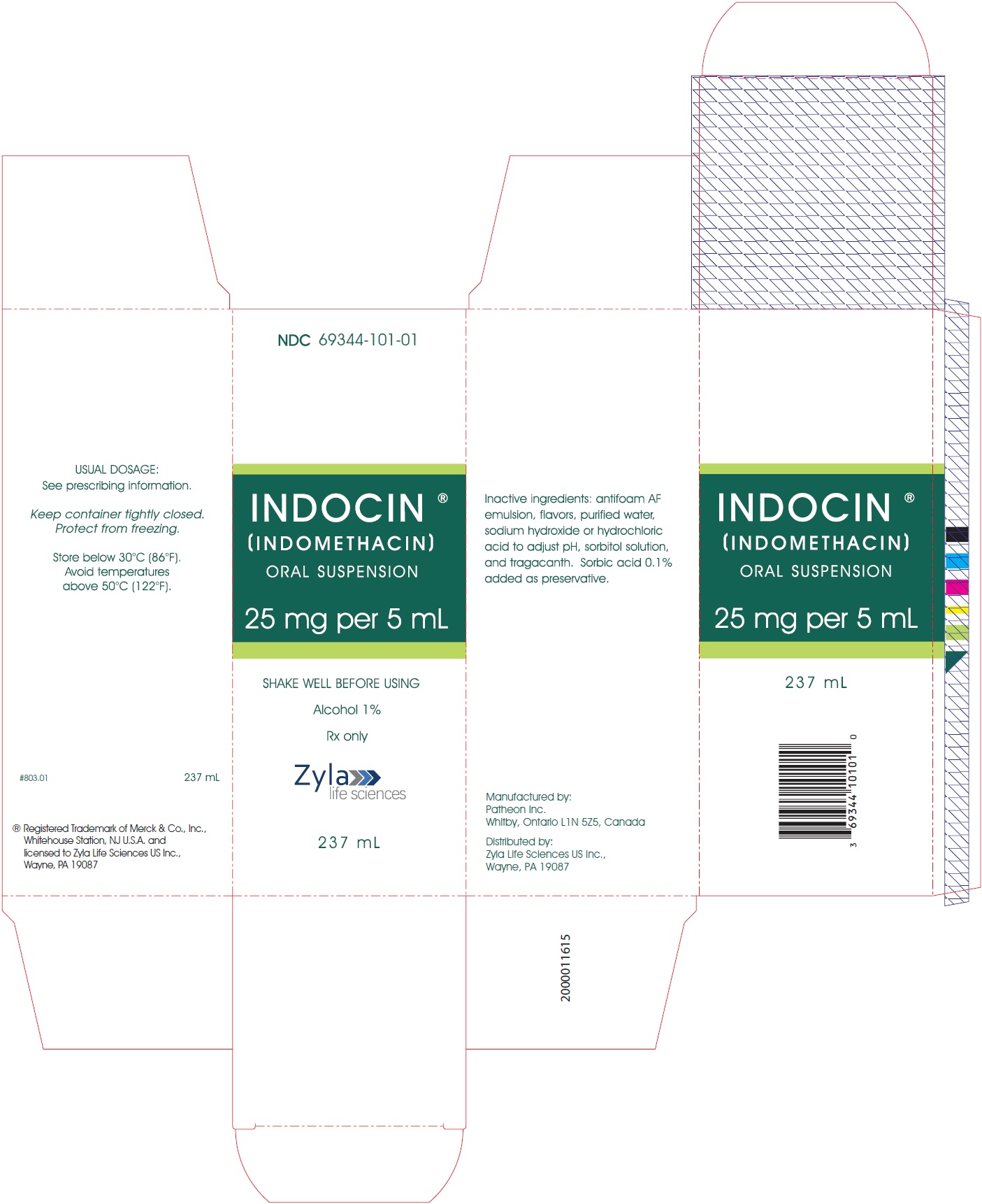 DRUG LABEL: Indocin
NDC: 69344-101 | Form: SUSPENSION
Manufacturer: Zyla Life Sciences US LLC
Category: prescription | Type: HUMAN PRESCRIPTION DRUG LABEL
Date: 20241216

ACTIVE INGREDIENTS: INDOMETHACIN 25 mg/5 mL
INACTIVE INGREDIENTS: WATER; SODIUM HYDROXIDE; HYDROCHLORIC ACID; SORBITOL; TRAGACANTH; ALCOHOL; SORBIC ACID

HIGHLIGHTS OF PRESCRIBING INFORMATION

These highlights do not include all the information needed to use INDOCIN® ORAL SUSPENSION safely and effectively. See full prescribing information for INDOCIN.
INDOCIN (indomethacin) Oral Suspension, for oral use
Initial U.S. Approval: 1965

RECENT MAJOR CHANGES

Warnings and Precautions (5.9) | 11/2024

WARNING: RISK OF SERIOUS CARDIOVASCULAR AND GASTROINTESTINAL EVENTS

See full prescribing information for complete boxed warning.

- Nonsteroidal anti-inflammatory drugs (NSAIDs) cause an increased risk of serious cardiovascular thrombotic events, including myocardial infarction and stroke, which can be fatal. This risk may occur early in treatment and may increase with duration of use (5.1)
- INDOCIN is contraindicated in the setting of coronary artery bypass graft (CABG) surgery (4, 5.1)
- NSAIDs cause an increased risk of serious gastrointestinal (GI) adverse events including bleeding, ulceration, and perforation of the stomach or intestines, which can be fatal. These events can occur at any time during use and without warning symptoms. Elderly patients and patients with a prior history of peptic ulcer disease and/or GI bleeding are at greater risk for serious GI events (5.2)

1 INDICATIONS AND USAGE

INDOCIN is a nonsteroidal anti-inflammatory drug indicated for:

- Moderate to severe rheumatoid arthritis including acute flares of chronic disease
- Moderate to severe ankylosing spondylitis
- Moderate to severe osteoarthritis
- Acute painful shoulder (bursitis and/or tendinitis)
- Acute gouty arthritis (1)

2 DOSAGE AND ADMINISTRATION

- Use the lowest effective dosage for shortest duration consistent with individual patient treatment goals (2.1)
- The dosage for moderate to severe rheumatoid arthritis including acute flares of chronic disease; moderate to severe ankylosing spondylitis; and moderate to severe osteoarthritis is INDOCIN 25 mg (5 mL) two or three times a day (2.2)
- The dosage for acute painful shoulder (bursitis and/or tendinitis) is 75-150 mg (15-30 mL) daily in 3 or 4 divided doses (2.3)
- The dosage for acute gouty arthritis is INDOCIN 50 mg (10 mL) three times a day (2.4)

3 DOSAGE FORMS AND STRENGTHS

INDOCIN (indomethacin) Oral Suspension: 25 mg of indocmethacin per 5mL (3)

4 CONTRAINDICATIONS

- Known hypersensitivity to indomethacin or any components of the drug product (4)
- History of asthma, urticaria, or other allergic-type reactions after taking aspirin or other NSAIDs (4)
- In the setting of CABG surgery (4)

5 WARNINGS AND PRECAUTIONS

- Hepatotoxicity: Inform patients of warning signs and symptoms of hepatotoxicity. Discontinue if abnormal liver tests persist or worsen or if clinical signs and symptoms of liver disease develop (5.3)
- Hypertension: Patients taking some antihypertensive medications may have impaired response to these therapies when taking NSAIDs. Monitor blood pressure (5.4, 7)
- Heart Failure and Edema: Avoid use of INDOCIN in patients with severe heart failure unless benefits are expected to outweigh risk of worsening heart failure (5.5)
- Renal Toxicity: Monitor renal function in patients with renal or hepatic impairment, heart failure, dehydration, or hypovolemia. Avoid use of INDOCIN in patients with advanced renal disease unless benefits are expected to outweigh risk of worsening renal function (5.6)
- Anaphylactic Reactions: Seek emergency help if an anaphylactic reaction occurs (5.7)
- Exacerbation of Asthma Related to Aspirin Sensitivity: INDOCIN is contraindicated in patients with aspirin-sensitive asthma. Monitor patients with preexisting asthma (without aspirin sensitivity) (5.8)
- Serious Skin Reactions: Discontinue INDOCIN at first appearance of skin rash or other signs of hypersensitivity (5.9)
- Drug Reaction with Eosinophilia and Systemic Symptoms (DRESS):
  Discontinue and evaluate clinically (5.10)
- Fetal Toxicity: Limit use of NSAIDs, including INDOCIN, between
  about 20 to 30 weeks in pregnancy due to the risk of
  oligohydramnios/fetal renal dysfunction. Avoid use of NSAIDs in
  women at about 30 weeks gestation and later in pregnancy due to the
  risks of oligohydramnios/fetal dysfunction and premature closure of the
  fetal ductus arteriosus (5.11, 8.1)
- Hematologic Toxicity: Monitor hemoglobin or hematocrit in patients with any signs or symptoms of anemia (5.12, 7)

6 ADVERSE REACTIONS

Most common adverse reactions (incidence ≥ 3%) are headache, dizziness, dyspepsia, and nausea. (6)

To report SUSPECTED ADVERSE REACTIONS, contact Zyla Life Sciences US Inc., at 1-800-518-1084 or FDA at 1-800-FDA-1088 or www.fda.gov/medwatch.

7 DRUG INTERACTIONS

- Drugs that Interfere with Hemostasis (e.g. warfarin, aspirin, SSRIs/SNRIs): Monitor patients for bleeding who are concomitantly taking INDOCIN with drugs that interfere with hemostasis. Concomitant use of INDOCIN and analgesic doses of aspirin is not generally recommended (7)
- ACE Iinhibitors, Angiotensin Receptor Blockers (ARB), or Beta-Blockers: Concomitant use with INDOCIN may diminish the antihypertensive effect of these drugs. Monitor blood pressure (7)
- ACE Inhibitors and ARBs: Concomitant use with INDOCIN in elderly, volume depleted, or those with renal impairment may result in deterioration of renal function. In such high risk patients, monitor for signs of worsening renal function (7)
- Diuretics: NSAIDs can reduce natriuretic effect of furosemide and thiazide diuretics. Monitor patients to assure diuretic efficacy including antihypertensive effects (7)
- Digoxin: Concomitant use with INDOCIN can increase serum concentration and prolong half-life of digoxin. Monitor serum digoxin levels (7)

8 USE IN SPECIFIC POPULATIONS

- Infertility: NSAIDs are associated with reversible infertility. Consider withdrawal of INDOCIN in women who have difficulties conceiving (8.3)

FULL PRESCRIBING INFORMATION

WARNING: RISK OF SERIOUS CARDIOVASCULAR AND GASTROINTESTINAL EVENTS

Cardiovascular Thrombotic Events

- Nonsteroidal anti-inflammatory drugs (NSAIDs) cause an increased risk of serious cardiovascular thrombotic events, including myocardial infarction and stroke, which can be fatal. This risk may occur early in treatment and may increase with duration of use [see Warnings and Precautions (5.1)].
- INDOCIN is contraindicated in the setting of coronary artery bypass graft (CABG) surgery [see Contraindications (4) and Warnings and Precautions (5.1)].

Gastrointestinal Bleeding, Ulceration, and Perforation

- NSAIDs cause an increased risk of serious gastrointestinal (GI) adverse events including bleeding, ulceration, and perforation of the stomach or intestines, which can be fatal. These events can occur at any time during use and without warning symptoms. Elderly patients and patients with a prior history of peptic ulcer disease and/or GI bleeding are at greater risk for serious GI events [see Warnings and Precautions (5.2)].

1 INDICATIONS AND USAGE

INDOCIN Oral Suspension is indicated for:

- Moderate to severe rheumatoid arthritis including acute flares of chronic disease
- Moderate to severe ankylosing spondylitis
- Moderate to severe osteoarthritis
- Acute painful shoulder (bursitis and/or tendinitis)
- Acute gouty arthritis

2 DOSAGE AND ADMINISTRATION

2.1 General Dosing Instructions

Carefully consider the potential benefits and risks of INDOCIN and other treatment options before deciding to use INDOCIN. Use the lowest effective dosage for the shortest duration consistent with individual patient treatment goals [see Warnings and Precautions (5)].

After observing the response to initial therapy with indomethacin, the dose and frequency should be adjusted to suit an individual patient’s needs.

Adverse reactions generally appear to correlate with the dose of indomethacin. Therefore, every effort should be made to determine the lowest effective dosage for the individual patient.

Dosage recommendations for active stages of the following:

2.2 Moderate to severe rheumatoid arthritis including acute flares of chronic disease; moderate to severe ankylosing spondylitis; and moderate to severe osteoarthritis

INDOCIN 25 mg (5 mL) twice a day or three times a day. If this is well tolerated, increase the daily dosage by 25 mg (5 mL) or by 50 mg (10 mL), if required by continuing symptoms, at weekly intervals until a satisfactory response is obtained or until a total daily dose of 150- 200 mg (30 - 40 mL) is reached. Doses above this amount generally do not increase the effectiveness of the drug.

In patients who have persistent night pain and/or morning stiffness, the giving of a large portion, up to a maximum of 100 mg (20 mL), of the total daily dose at bedtime may be helpful in affording relief. The total daily dose should not exceed 200 mg (40 mL). In acute flares of chronic rheumatoid arthritis, it may be necessary to increase the dosage by 25 mg (5 mL) or, if required, by 50 mg (10 mL) daily.

If minor adverse effects develop as the dosage is increased, reduce the dosage rapidly to a tolerated dose and observe the patient closely.

If severe adverse reactions occur, stop the drug. After the acute phase of the disease is under control, an attempt to reduce the daily dose should be made repeatedly until the patient is receiving the smallest effective dose or the drug is discontinued.

Careful instructions to, and observations of, the individual patient are essential to the prevention of serious, irreversible, including fatal, adverse reactions.

As advancing years appear to increase the possibility of adverse reactions, INDOCIN should be used with greater care in the elderly [see Use in Specific Populations (8.5)].

2.3 Acute painful shoulder (bursitis and/or tendinitis)

INDOCIN 75-150 mg (15-30 mL) daily in 3 or 4 divided doses.
The drug should be discontinued after the signs and symptoms of inflammation have been controlled for several days. The usual course of therapy is 7-14 days.

2.4 Acute Gouty Arthritis

INDOCIN 50 mg (10 mL) three times a day until pain is tolerable. The dose should then be rapidly reduced to complete cessation of the drug. Definite relief of pain has been reported within 2 to 4 hours. Tenderness and heat usually subside in 24 to 36 hours, and swelling gradually disappears in 3 to 5 days.

3 DOSAGE FORMS AND STRENGTHS

INDOCIN (indomethacin) Oral Suspension 25 mg per 5 mL, is an off-white suspension with a pineapple coconut mint flavor.

4 CONTRAINDICATIONS

INDOCIN is contraindicated in the following patients:

- Known hypersensitivity (e.g., anaphylactic reactions and serious skin reactions) to indomethacin or any components of the drug product [see Warnings and Precautions (5.7, 5.9)]
- History of asthma, urticaria, or other allergic-type reactions after taking aspirin or other NSAIDs. Severe, sometimes fatal, anaphylactic reactions to NSAIDs have been reported in such patients [see Warnings and Precautions (5.7, 5.8)]
- In the setting of coronary artery bypass graft (CABG) surgery [see Warnings and Precautions (5.1)]

5 WARNINGS AND PRECAUTIONS

5.1 Cardiovascular Thrombotic Events

Clinical trials of several COX-2 selective and nonselective NSAIDs of up to three years duration have shown an increased risk of serious cardiovascular (CV) thrombotic events, including myocardial infarction (MI) and stroke, which can be fatal. Based on available data, it is unclear that the risk for CV thrombotic events is similar for all NSAIDs. The relative increase in serious CV thrombotic events over baseline conferred by NSAID use appears to be similar in those with and without known CV disease or risk factors for CV disease. However, patients with known CV disease or risk factors had a higher absolute incidence of excess serious CV thrombotic events, due to their increased baseline rate. Some observational studies found that this increased risk of serious CV thrombotic events began as early as the first weeks of treatment. The increase in CV thrombotic risk has been observed most consistently at higher doses.

To minimize the potential risk for an adverse CV event in NSAID-treated patients, use the lowest effective dose for the shortest duration possible. Physicians and patients should remain alert for the development of such events, throughout the entire treatment course, even in the absence of previous CV symptoms. Patients should be informed about the symptoms of serious CV events and the steps to take if they occur.

There is no consistent evidence that concurrent use of aspirin mitigates the increased risk of serious CV thrombotic events associated with NSAID use. The concurrent use of aspirin and an NSAID, such as indomethacin, increases the risk of serious gastrointestinal (GI) events [see Warnings and Precautions (5.2)].

Status Post Coronary Artery Bypass Graft (CABG) Surgery
Two large, controlled clinical trials of a COX-2 selective NSAID for the treatment of pain in the first 10–14 days following CABG surgery found an increased incidence of myocardial infarction and stroke. NSAIDs are contraindicated in the setting of CABG [see Contraindications (4)].

Post-MI Patients
Observational studies conducted in the Danish National Registry have demonstrated that patients treated with NSAIDs in the post-MI period were at increased risk of reinfarction, CV-related death, and all-cause mortality beginning in the first week of treatment. In this same cohort, the incidence of death in the first year post-MI was 20 per 100 person years in NSAID-treated patients compared to 12 per 100 person years in non-NSAID exposed patients. Although the absolute rate of death declined somewhat after the first year post-MI, the increased relative risk of death in NSAID users persisted over at least the next four years of follow-up.

Avoid the use of INDOCIN in patients with a recent MI unless the benefits are expected to outweigh the risk of recurrent CV thrombotic events. If INDOCIN is used in patients with a recent MI, monitor patients for signs of cardiac ischemia.

5.2 Gastrointestinal Bleeding, Ulceration, and Perforation

NSAIDs, including indomethacin, cause serious gastrointestinal (GI) adverse events including inflammation, bleeding, ulceration, and perforation of the esophagus, stomach, small intestine, or large intestine, which can be fatal. These serious adverse events can occur at any time, with or without warning symptoms, in patients treated with NSAIDs. Only one in five patients who develop a serious upper GI adverse event on NSAID therapy is symptomatic. Upper GI ulcers, gross bleeding, or perforation caused by NSAIDs occurred in approximately 1% of patients treated for 3-6 months, and in about 2%-4% of patients treated for one year. However, even short-term NSAID therapy is not without risk.

Risk Factors for GI Bleeding, Ulceration, and Perforation
Patients with a prior history of peptic ulcer disease and/or GI bleeding who used NSAIDs had a greater than 10-fold increased risk for developing a GI bleed compared to patients without these risk factors. Other factors that increase the risk of GI bleeding in patients treated with NSAIDs include longer duration of NSAID therapy; concomitant use of oral corticosteroids, aspirin, anticoagulants, or selective serotonin reuptake inhibitors (SSRIs); smoking; use of alcohol; older age; and poor general health status. Most postmarketing reports of fatal GI events occurred in elderly or debilitated patients. Additionally, patients with advanced liver disease and/or coagulopathy are at increased risk for GI bleeding.

Strategies to Minimize the GI Risks in NSAID-treated patients:

- Use the lowest effective dosage for the shortest possible duration.
- Avoid administration of more than one NSAID at a time.
- Avoid use in patients at higher risk unless benefits are expected to outweigh the increased risk of bleeding. For such patients, as well as those with active GI bleeding, consider alternate therapies other than NSAIDs.
- Remain alert for signs and symptoms of GI ulceration and bleeding during NSAID therapy.
- If a serious GI adverse event is suspected, promptly initiate evaluation and treatment, and discontinue INDOCIN until a serious GI adverse event is ruled out.
- In the setting of concomitant use of low-dose aspirin for cardiac prophylaxis, monitor patients more closely for evidence of GI bleeding [see Drug Interactions (7)].

5.3 Hepatotoxicity

Elevations of ALT or AST (three or more times the upper limit of normal [ULN]) have been reported in approximately 1% of NSAID-treated patients in clinical trials. In addition, rare, sometimes fatal, cases of severe hepatic injury, including fulminant hepatitis, liver necrosis, and hepatic failure have been reported.

Elevations of ALT or AST (less than three times ULN) may occur in up to 15% of patients treated with NSAIDs including indomethacin.

Inform patients of the warning signs and symptoms of hepatotoxicity (e.g., nausea, fatigue, lethargy, diarrhea, pruritus, jaundice, right upper quadrant tenderness, and "flu-like" symptoms). If clinical signs and symptoms consistent with liver disease develop, or if systemic manifestations occur (e.g., eosinophilia, rash, etc.), discontinue INDOCIN immediately, and perform a clinical evaluation of the patient.

5.4 Hypertension

NSAIDs, including INDOCIN, can lead to new onset of hypertension or worsening of preexisting hypertension, either of which may contribute to the increased incidence of CV events. Patients taking angiotensin converting enzyme (ACE) inhibitors, thiazide diuretics, or loop diuretics may have impaired response to these therapies when taking NSAIDs [see Drug Interactions (7)].

Monitor blood pressure (BP) during the initiation of NSAID treatment and throughout the course of therapy.

5.5 Heart Failure and Edema

The Coxib and traditional NSAID Trialists’ Collaboration meta-analysis of randomized controlled trials demonstrated an approximately two-fold increase in hospitalizations for heart failure in COX-2 selective-treated patients and nonselective NSAID-treated patients compared to placebo-treated patients. In a Danish National Registry study of patients with heart failure, NSAID use increased the risk of MI, hospitalization for heart failure, and death.

Additionally, fluid retention and edema have been observed in some patients treated with NSAIDs. Use of indomethacin may blunt the CV effects of several therapeutic agents used to treat these medical conditions (e.g., diuretics, ACE inhibitors, or angiotensin receptor blockers [ARBs]) [see Drug Interactions (7)].

Avoid the use of INDOCIN in patients with severe heart failure unless the benefits are expected to outweigh the risk of worsening heart failure. If INDOCIN is used in patients with severe heart failure, monitor patients for signs of worsening heart failure.

5.6 Renal Toxicity and Hyperkalemia

Renal Toxicity
Long-term administration of NSAIDs has resulted in renal papillary necrosis and other renal injury.

Renal toxicity has also been seen in patients in whom renal prostaglandins have a compensatory role in the maintenance of renal perfusion. In these patients, administration of an NSAID may cause a dose-dependent reduction in prostaglandin formation and, secondarily, in renal blood flow, which may precipitate overt renal decompensation. Patients at greatest risk of this reaction are those with impaired renal function, dehydration, hypovolemia, heart failure, liver dysfunction, those taking diuretics and ACE inhibitors or ARBs, and the elderly. Discontinuation of NSAID therapy is usually followed by recovery to the pretreatment state.

No information is available from controlled clinical studies regarding the use of INDOCIN in patients with advanced renal disease. The renal effects of INDOCIN may hasten the progression of renal dysfunction in patients with preexisting renal disease.

Correct volume status in dehydrated or hypovolemic patients prior to initiating INDOCIN. Monitor renal function in patients with renal or hepatic impairment, heart failure, dehydration, or hypovolemia during use of INDOCIN [see Drug Interactions (7)]. Avoid the use of INDOCIN in patients with advanced renal disease unless the benefits are expected to outweigh the risk of worsening renal function. If INDOCIN is used in patients with advanced renal disease, monitor patients for signs of worsening renal function.

It has been reported that the addition of the potassium-sparing diuretic, triamterene, to a maintenance schedule of indomethacin resulted in reversible acute renal failure in two of four healthy volunteers. Indomethacin and triamterene should not be administered together.

Hyperkalemia
Increases in serum potassium concentration, including hyperkalemia, have been reported with use of NSAIDs, even in some patients without renal impairment. In patients with normal renal function, these effects have been attributed to a hyporeninemic-hypoaldosteronism state.

Both Indomethacin and potassium-sparing diuretics may be associated with increased serum potassium levels. The potential effects of indomethacin and potassium-sparing diuretics on potassium levels and renal function should be considered when these agents are administered concurrently.

5.7 Anaphylactic Reactions

Indomethacin has been associated with anaphylactic reactions in patients with and without known hypersensitivity to indomethacin and in patients with aspirin-sensitive asthma [see Contraindications (4) and Warnings and Precautions (5.8)].

Seek emergency help if an anaphylactic reaction occurs.

5.8 Exacerbation of Asthma Related to Aspirin Sensitivity

A subpopulation of patients with asthma may have aspirin-sensitive asthma which may include chronic rhinosinusitis complicated by nasal polyps; severe, potentially fatal bronchospasm; and/or intolerance to aspirin and other NSAIDs. Because cross-reactivity between aspirin and other NSAIDs has been reported in such aspirin-sensitive patients, INDOCIN is contraindicated in patients with this form of aspirin sensitivity [see Contraindications (4)]. When INDOCIN is used in patients with preexisting asthma (without known aspirin sensitivity), monitor patients for changes in the signs and symptoms of asthma.

5.9 Serious Skin Reactions

NSAIDs, including indomethacin, can cause serious skin adverse reactions such as exfoliative dermatitis, Stevens-Johnson Syndrome (SJS), and toxic epidermal necrolysis (TEN), which can be fatal. NSAIDs can also cause fixed drug eruption (FDE). FDE may present as a more severe variant known as generalized bullous fixed drug eruption (GBFDE), which can be life-threatening. These serious events may occur without warning. Inform patients about the signs and symptoms of serious skin reactions, and to discontinue the use of INDOCIN at the first appearance of skin rash or any other sign of hypersensitivity. INDOCIN is contraindicated in patients with previous serious skin reactions to NSAIDs [see Contraindications (4)].

5.10 Drug Reaction with Eosinophilia and Systemic Symptoms (DRESS)

Drug Reaction with Eosinophilia and Systemic Symptoms (DRESS) has been reported in patients taking NSAIDs such as INDOCIN. Some of these events have been fatal or lifethreatening. DRESS typically, although not exclusively, presents with fever, rash, lymphadenopathy, and/or facial swelling. Other clinical manifestations may include hepatitis, nephritis, hematological abnormalities, myocarditis, or myositis. Sometimes symptoms of DRESS may resemble an acute viral infection. Eosinophilia is often present. Because this disorder is variable in its presentation, other organ systems not noted here may be involved. It is important to note that early manifestations of hypersensitivity, such as fever or lymphadenopathy, may be present even though rash is not evident. If such signs or symptoms are present, discontinue INDOCIN and evaluate the patient immediately.

5.11 Fetal Toxicity

Premature Closure of Fetal Ductus Arteriosus

Avoid use of NSAIDS, including INDOCIN, in pregnant women at about 30 weeks of gestation and later. NSAIDs, including INDOCIN, increase the risk of premature closure of the fetal ductus arteriosus at approximately this gestational age.

Oligohydramnios/Neonatal Renal Impairment

Use of NSAIDs, including INDOCIN, at about 20 weeks gestation or later in pregnancy may cause fetal renal dysfunction leading to oligohydramnios and, in some cases, neonatal renal impairment. These adverse outcomes are seen, on average, after days to weeks of treatment, although oligohydramnios has been infrequently reported as soon as 48 hours after NSAID initiation.

Oligohydramnios is often, but not always, reversible with treatment discontinuation. Complications of prolonged oligohydramnios may, for example, include limb contractures and delayed lung maturation. In some postmarketing cases of impaired neonatal renal function, invasive procedures such as exchange transfusion or dialysis were required.

If NSAID treatment is necessary between about 20 weeks and 30 weeks gestation, limit INDOCIN use to the lowest effective dose and shortest duration possible. Consider ultrasound monitoring of amniotic fluid if INDOCIN treatment extends beyond 48 hours. Discontinue INDOCIN if oligohydramnios occurs and follow up according to clinical practice [see Use in Specific Populations (8.1)].

5.12 Hematologic Toxicity

Anemia has occurred in NSAID-treated patients. This may be due to occult or gross blood loss, fluid retention, or an incompletely described effect on erythropoiesis. If a patient treated with INDOCIN has any signs or symptoms of anemia, monitor hemoglobin or hematocrit.

NSAIDs, including INDOCIN, may increase the risk of bleeding events. Co-morbid conditions, such as coagulation disorders, or concomitant use of warfarin, other anticoagulants, antiplatelet agents (e.g., aspirin), serotonin reuptake inhibitors (SSRIs) and serotonin norepinephrine reuptake inhibitors (SNRIs) may increase this risk. Monitor these patients for signs of bleeding [see Drug Interactions (7)].

5.13 Masking of Inflammation and Fever

The pharmacological activity of INDOCIN in reducing inflammation, and possibly fever, may diminish the utility of diagnostic signs in detecting infections.

5.14 Laboratory Monitoring

Because serious GI bleeding, hepatotoxicity, and renal injury can occur without warning symptoms or signs, consider monitoring patients on long-term NSAID treatment with a CBC and a chemistry profile periodically [see Warnings and Precautions (5.2, 5.3, 5.6)].

5.15 Central Nervous System Effects

INDOCIN may aggravate depression or other psychiatric disturbances, epilepsy, and parkinsonism, and should be used with considerable caution in patients with these conditions. Discontinue INDOCIN if severe CNS adverse reactions develop.

INDOCIN may cause drowsiness; therefore, caution patients about engaging in activities requiring mental alertness and motor coordination, such as driving a car. Indomethacin may also cause headache. Headache which persists despite dosage reduction requires cessation of therapy with INDOCIN.

5.16 Ocular Effects

Corneal deposits and retinal disturbances, including those of the macula, have been observed in some patients who had received prolonged therapy with INDOCIN. Be alert to the possible association between the changes noted and INDOCIN. It is advisable to discontinue therapy if such changes are observed. Blurred vision may be a significant symptom and warrants a thorough ophthalmological examination. Since these changes may be asymptomatic, ophthalmologic examination at periodic intervals is desirable in patients receiving prolonged therapy. INDOCIN is not indicated for long-term treatment.

6 ADVERSE REACTIONS

The following adverse reactions are discussed in greater detail in other sections of the labeling:

- Cardiovascular Thrombotic Events [see Warnings and Precautions (5.1)]
- GI Bleeding, Ulceration and Perforation [see Warnings and Precautions (5.2)]
- Hepatotoxicity [see Warnings and Precautions (5.3)]
- Hypertension [see Warnings and Precautions (5.4)]
- Heart Failure and Edema [see Warnings and Precautions (5.5)]
- Renal Toxicity and Hyperkalemia [see Warnings and Precautions (5.6)]
- Anaphylactic Reactions [see Warnings and Precautions (5.7)]
- Serious Skin Reactions [see Warnings and Precautions (5.9)]
- Hematologic Toxicity [see Warnings and Precautions (5.12)]

6.1 Clinical Trials Experience

Because clinical trials are conducted under widely varying conditions, adverse reaction rates observed in the clinical trials of a drug cannot be directly compared to rates in the clinical trials of another drug and may not reflect the rates observed in clinical practice.

In a gastroscopic study in 45 healthy subjects, the number of gastric mucosal abnormalities was significantly higher in the group receiving INDOCIN Capsules than in the group taking INDOCIN Suppositories or placebo.

In a double-blind comparative clinical study involving 175 patients with rheumatoid arthritis, however, the incidence of upper gastrointestinal adverse effects with INDOCIN Suppositories or Capsules was comparable. The incidence of lower gastrointestinal adverse effects was greater in the suppository group.

The adverse reactions for INDOCIN Capsules listed in the following table have been arranged into two groups: (1) incidence greater than 1%; and (2) incidence less than 1%. The incidence for group (1) was obtained from 33 double-blind controlled clinical trials reported in the literature (1,092 patients). The incidence for group (2) was based on reports in clinical trials, in the literature, and on voluntary reports since marketing. The probability of a causal relationship exists between INDOCIN and these adverse reactions, some of which have been reported only rarely.

The adverse reactions reported with INDOCIN Capsules may also occur with use of the suspension.

Table 1 Summary of Adverse Reactions for INDOCIN Capsules
Incidence greater than 1% | Incidence less than 1%
GASTROINTESTINAL
nausea* with or without vomiting dyspepsia* (including indigestion, heartburn and epigastric pain) diarrhea abdominal distress or pain constipation | anorexia bloating (includes distension) flatulence peptic ulcer gastroenteritis rectal bleeding proctitis single or multiple ulcerations, including perforation and hemorrhage of the esophagus, stomach, duodenum or small and large intestines intestinal ulceration associated with stenosis and obstruction | gastrointestinal bleeding without obvious ulcer formation and perforation of preexisting sigmoid lesions (diverticulum, carcinoma, etc.) development of ulcerative colitis and regional ileitis ulcerative stomatitis toxic hepatitis and jaundice (some fatal cases have been reported) intestinal strictures (diaphragms) pancreatitis
CENTRAL NERVOUS SYSTEM
headache (11.7%) dizziness* vertigo depression and fatigue (including malaise and listlessness) | anxiety (includes nervousness) muscle weakness involuntary muscle movements insomnia muzziness psychic disturbances including psychotic episodes mental confusion drowsiness | light-headedness syncope paresthesia aggravation of epilepsy and parkinsonism depersonalization coma peripheral neuropathy convulsion dysarthria
SPECIAL SENSES
tinnitus | ocular — corneal deposits and retinal disturbances, including those of the macula, have been reported in some patients on prolonged therapy with INDOCIN | blurred vision diplopia hearing disturbances, deafness
CARDIOVASCULAR
None | hypertension hypotension tachycardia chest pain | congestive heart failure arrhythmia; palpitations
METABOLIC
None | edema weight gain fluid retention flushing or sweating | hyperglycemia glycosuria hyperkalemia
INTEGUMENTARY
none | pruritus rash; urticaria petechiae or ecchymosis | exfoliative dermatitis erythema nodosum loss of hair Stevens-Johnson syndrome erythema multiforme toxic epidermal necrolysis
HEMATOLOGIC
None | leukopenia bone marrow depression anemia secondary to obvious or occult gastrointestinal bleeding | aplastic anemia hemolytic anemia agranulocytosis thrombocytopenic purpura disseminated intravascular coagulation
HYPERSENSITIVITY
None | acute anaphylaxis acute respiratory distress rapid fall in blood pressure resembling a shock-like state angioedema | dyspnea asthma purpura angiitis pulmonary edema fever
GENITOURINARY
None | hematuria vaginal bleeding proteinuria nephrotic syndrome interstitial nephritis | BUN elevation renal insufficiency, including renal failure
MISCELLANEOUS
None | epistaxis breast changes, including enlargement and tenderness, or gynecomastia
* Reactions occurring in 3% to 9% of patients treated with INDOCIN. (Those reactions occurring in less than 3% of the patients are unmarked.)

Causal relationship unknown: Other reactions have been reported but occurred under circumstances where a causal relationship could not be established. However, in these rarely reported events, the possibility cannot be excluded. Therefore, these observations are being listed to serve as alerting information to physicians:

Cardiovascular: Thrombophlebitis

Hematologic: Although there have been several reports of leukemia, the supporting information is weak

Genitourinary: Urinary frequency

A rare occurrence of fulminant necrotizing fasciitis, particularly in association with Group Aβ hemolytic streptococcus, has been described in persons treated with nonsteroidal anti-inflammatory agents, including indomethacin, sometimes with fatal outcome

6.2 Postmarketing Experience

The following adverse reactions have been identified during postapproval use of indomethacin. Because these reactions are reported voluntarily from a population of uncertain size, it is not always possible to reliably estimate their frequency or establish a causal relationship to drug exposure.

Skin and Appendages: Exfoliative dermatitis, Stevens-Johnson Syndrome (SJS), toxic epidermal necrolysis (TEN), and fixed drug eruption (FDE).

7 DRUG INTERACTIONS

See Table 2 for clinically significant drug interactions with indomethacin.

Table 2 Clinically Significant Drug Interactions with Indomethacin
Drugs That Interfere with Hemostasis
Clinical Impact: | - Indomethacin and anticoagulants such as warfarin have a synergistic effect on bleeding. The concomitant use of indomethacin and anticoagulants have an increased risk of serious bleeding compared to the use of either drug alone. - Serotonin release by platelets plays an important role in hemostasis. Case-control and cohort epidemiological studies showed that concomitant use of drugs that interfere with serotonin reuptake and an NSAID may potentiate the risk of bleeding more than an NSAID alone.
Intervention: | Monitor patients with concomitant use of INDOCIN with anticoagulants (e.g., warfarin), antiplatelet agents (e.g., aspirin), selective serotonin reuptake inhibitors (SSRIs), and serotonin norepinephrine reuptake inhibitors (SNRIs) for signs of bleeding [see Warnings and Precautions (5.12) ].
Aspirin
Clinical Impact | Controlled clinical studies showed that the concomitant use of NSAIDs and analgesic doses of aspirin does not produce any greater therapeutic effect than the use of NSAIDs alone. In a clinical study, the concomitant use of an INDOCIN and aspirin was associated with a significantly increased incidence of GI adverse reactions as compared to use of the INDOCIN alone [see Warnings and Precautions (5.2) ].
Intervention: | Concomitant use of INDOCIN and analgesic doses of aspirin is not generally recommended because of the increased risk of bleeding [see Warnings and Precautions (5.12)]. INDOCIN is not a substitute for low dose aspirin for cardiovascular protection.
ACE Inhibitors, Angiotensin Receptor Blockers, and Beta-Blockers
Clinical Impact: | - NSAIDs may diminish the antihypertensive effect of angiotensin converting enzyme (ACE) inhibitors, angiotensin receptor blockers (ARBs), or beta-blockers (including propranolol). - In patients who are elderly, volume-depleted (including those on diuretic therapy), or have renal impairment, co-administration of an NSAID with ACE inhibitors or ARBs may result in deterioration of renal function, including possible acute renal failure. These effects are usually reversible.
Intervention: | - During concomitant use of INDOCIN and ACE-inhibitors, ARBs, or beta-blockers, monitor blood pressure to ensure that the desired blood pressure is obtained. - During concomitant use of INDOCIN and ACE-inhibitors or ARBs in patients who are elderly, volume-depleted, or have impaired renal function, monitor for signs of worsening renal function [see Warnings and Precautions (5.6)]. - When these drugs are administered concomitantly, patients should be adequately hydrated. Assess renal function at the beginning of the concomitant treatment and periodically thereafter.
Diuretics
Clinical Impact: | Clinical studies, as well as post-marketing observations, showed that NSAIDs reduced the natriuretic effect of loop diuretics (e.g., furosemide) and thiazide diuretics in some patients. This effect has been attributed to the NSAID inhibition of renal prostaglandin synthesis. It has been reported that the addition of triamterene to a maintenance schedule of INDOCIN resulted in reversible acute renal failure in two of four healthy volunteers. INDOCIN and triamterene should not be administered together. Both INDOCIN and potassium-sparing diuretics may be associated with increased serum potassium levels. The potential effects of INDOCIN and potassium-sparing diuretics on potassium levels and renal function should be considered when these agents are administered concurrently.
Intervention: | Indomethacin and triamterene should not be administered together. During concomitant use of INDOCIN with diuretics, observe patients for signs of worsening renal function, in addition to assuring diuretic efficacy including antihypertensive effects. Be aware that indomethacin and potassium-sparing diuretics may both be associated with increased serum potassium levels [see Warnings and Precautions (5.6)].
Digoxin
Clinical Impact: | The concomitant use of INDOCIN with digoxin has been reported to increase the serum concentration and prolong the half-life of digoxin.
Intervention: | During concomitant use of INDOCIN and digoxin, monitor serum digoxin levels.
Lithium
Clinical Impact: | NSAIDs have produced elevations in plasma lithium levels and reductions in renal lithium clearance. The mean minimum lithium concentration increased 15%, and the renal clearance decreased by approximately 20%. This effect has been attributed to NSAID inhibition of renal prostaglandin synthesis
Intervention: | During concomitant use of INDOCIN and lithium, monitor patients for signs of lithium toxicity.
Methotrexate
Clinical Impact: | Concomitant use of NSAIDs and methotrexate may increase the risk for methotrexate toxicity (e.g., neutropenia, thrombocytopenia, renal dysfunction).
Intervention: | During concomitant use of INDOCIN and methotrexate, monitor patients for methotrexate toxicity.
Cyclosporine
Clinical Impact: | Concomitant use of INDOCIN and cyclosporine may increase cyclosporine’s nephrotoxicity.
Intervention: | During concomitant use of INDOCIN and cyclosporine, monitor patients for signs of worsening renal function.
NSAIDs and Salicylates
Clinical Impact: | Concomitant use of indomethacin with other NSAIDs or salicylates (e.g., diflunisal, salsalate) increases the risk of GI toxicity, with little or no increase in efficacy [see Warnings and Precautions (5.2)]. Combined use with diflunisal may be particularly hazardous because diflunisal causes significantly higher plasma levels of indomethacin [ see Clinical Pharmacology (12.3) ]. In some patients, combined use of indomethacin and diflunisal has been associated with fatal gastrointestinal hemorrhage.
Intervention: | The concomitant use of indomethacin with other NSAIDs or salicylates, especially diflunisal, is not recommended.
Pemetrexed
Clinical Impact: | Concomitant use of INDOCIN and pemetrexed may increase the risk of pemetrexed-associated myelosuppression, renal, and GI toxicity (see the pemetrexed prescribing information).
Intervention: | During concomitant use of INDOCIN and pemetrexed, in patients with renal impairment whose creatinine clearance ranges from 45 to 79 mL/min, monitor for myelosuppression, renal and GI toxicity. NSAIDs with short elimination half-lives (e.g., diclofenac, indomethacin) should be avoided for a period of two days before, the day of, and two days following administration of pemetrexed. In the absence of data regarding potential interaction between pemetrexed and NSAIDs with longer half-lives (e.g., meloxicam, nabumetone), patients taking these NSAIDs should interrupt dosing for at least five days before, the day of, and two days following pemetrexed administration.
Probenecid
Clinical Impact: | When indomethacin is given to patients receiving probenecid, the plasma levels of indomethacin are likely to be increased.
Intervention: | During the concomitant use of INDOCIN and probenecid, a lower total daily dosage of indomethacin may produce a satisfactory therapeutic effect. When increases in the dose of indomethacin are made, they should be made carefully and in small increments.

Effects on Laboratory Tests

INDOCIN reduces basal plasma renin activity (PRA), as well as those elevations of PRA induced by furosemide administration, or salt or volume depletion. These facts should be considered when evaluating plasma renin activity in hypertensive patients.

False-negative results in the dexamethasone suppression test (DST) in patients being treated with indomethacin have been reported. Thus, results of the DST should be interpreted with caution in these patients.

8 USE IN SPECIFIC POPULATIONS

8.1 Pregnancy

Risk Summary

Use of NSAIDs, including INDOCIN, can cause premature closure of the fetal ductus arteriosus and fetal renal dysfunction leading to oligohydramnios and, in some cases, neonatal renal impairment. Because of these risks, limit dose and duration of INDOCIN use between about 20 and 30 weeks of gestation, and avoid INDOCIN use at about 30 weeks of gestation and later in pregnancy (see Clinical Considerations, Data).

Premature Closure of Fetal Ductus Arteriosus

Use of NSAIDS, including INDOCIN, at about 30 weeks gestation or later in pregnancy increases the risk of premature closure of the fetal ductus arteriosus.

Oligohydramnios/Neonatal Renal Impairment

Use of NSAIDs at about 20 weeks gestation or later in pregnancy has been associated with cases of fetal renal dysfunction leading to oligohydramnios, and in some cases, neonatal renal impairment.

Data from observational studies regarding other potential embryofetal risks of NSAID use in women in the first or second trimesters of pregnancy are inconclusive. In animal reproduction studies retarded fetal ossification was observed with administration of indomethacin to mice and rats during organogenesis at doses 0.1 and 0.2 times, respectively, the maximum recommended human dose (MRHD, 200 mg (40mL)). In published studies in pregnant mice, indomethacin produced maternal toxicity and death, increased fetal resorptions, and fetal malformations at 0.1 times the MRHD. When rat and mice dams were dosed during the last three days of gestation, indomethacin produced neuronal necrosis in the offspring at 0.1 and 0.05 times the MRHD, respectively [see Data]. Based on animal data, prostaglandins have been shown to have an important role in endometrial vascular permeability, blastocyst implantation, and decidualization. In animal studies, administration of prostaglandin synthesis inhibitors such as indomethacin, resulted in increased pre- and post-implantation loss. Prostaglandins also have been shown to have an important role in fetal kidney development. In published animal studies, prostaglandin synthesis inhibitors have been reported to impair kidney development when administered at clinically relevant doses.

The estimated background risk of major birth defects and miscarriage for the indicated population(s) is unknown. All pregnancies have a background risk of birth defect, loss, or other adverse outcomes. In the U.S. general population, the estimated background risk of major birth defects and miscarriage in clinically recognized pregnancies is 2% to 4% and 15% to 20%, respectively.

Clinical Considerations

Fetal/Neonatal Adverse Reactions

Premature Closure of Fetal Ductus Arteriosus:

Avoid use of NSAIDs in women at about 30 weeks gestation and later in pregnancy, because NSAIDs, including INDOCIN, can cause premature closure of the fetal ductus arteriosus (see Data).

Oligohydramnios/Neonatal Renal Impairment:

If an NSAID is necessary at about 20 weeks gestation or later in pregnancy, limit the use to the lowest effective dose and shortest duration possible. If INDOCIN treatment extends beyond 48 hours, consider monitoring with ultrasound for oligohydramnios. If oligohydramnios occurs, discontinue INDOCIN and follow up according to clinical practice (see Data).

Data

Human Data

Premature Closure of Fetal Ductus Arteriosus:

Published literature reports that the use of NSAIDs at about 30 weeks of gestation and later in pregnancy may cause premature closure of the fetal ductus arteriosus.

Oligohydramnios/Neonatal Renal Impairment:

Published studies and postmarketing reports describe maternal NSAID use at about 20 weeks gestation or later in pregnancy associated with fetal renal dysfunction leading to oligohydramnios, and in some cases, neonatal renal impairment. These adverse outcomes are seen, on average, after days to weeks of treatment, although oligohydramnios has been infrequently reported as soon as 48 hours after NSAID initiation. In many cases, but not all, the decrease in amniotic fluid was transient and reversible with cessation of the drug. There have been a limited number of case reports of maternal NSAID use and neonatal renal dysfunction without oligohydramnios, some of which were irreversible. Some cases of neonatal renal dysfunction required treatment with invasive procedures, such as exchange transfusion or dialysis.

Methodological limitations of these postmarketing studies and reports include lack of a control group; limited information regarding dose, duration, and timing of drug exposure; and concomitant use of other medications. These limitations preclude establishing a reliable estimate of the risk of adverse fetal and neonatal outcomes with maternal NSAID use. Because the published safety data on neonatal outcomes involved mostly preterm infants, the generalizability of certain reported risks to the full-term infant exposed to NSAIDs through maternal use is uncertain.

Animal data

Reproductive studies were conducted in mice and rats at dosages of 0.5, 1.0, 2.0, and 4.0 mg/kg/day. Except for retarded fetal ossification at 4 mg/kg/day (0.1 times [mice] and 0.2 times [rats] the MRHD on a mg/m^2 basis, respectively) considered secondary to the decreased average fetal weights, no increase in fetal malformations was observed as compared with control groups. Other studies in mice reported in the literature using higher doses (5 to 15 mg/kg/day, 0.1 to 0.4 times MRHD on a mg/m^2 basis) have described maternal toxicity and death, increased fetal resorptions, and fetal malformations.

In rats and mice, maternal indomethacin administration of 4.0 mg/kg/day (0.2 times and 0.1 times the MRHD on a mg/m^2 basis) during the last 3 days of gestation was associated with an increased incidence of neuronal necrosis in the diencephalon in the live-born fetuses however no increase in neuronal necrosis was observed at 2.0 mg/kg/day as compared to the control groups (0.1 times and 0.05 times the MRHD on a mg/m^2 basis). Administration of 0.5 or 4.0 mg/kg/day to offspring during the first 3 days of life did not cause an increase in neuronal necrosis at either dose level.

8.2 Lactation

Risk Summary

Based on available published clinical data, indomethacin may be present in human milk. The developmental and health benefits of breastfeeding should be considered along with the mother’s clinical need for INDOCIN and any potential adverse effects on the breastfed infant from the INDOCIN or from the underlying maternal condition.

Data

In one study, levels of indomethacin in breast milk were below the sensitivity of the assay (<20 mcg/L) in 11 of 15 women using doses ranging from 75 mg orally to 300 mg rectally daily (0.94 to 4.29 mg/kg daily) in the postpartum period. Based on these levels, the average concentration present in breast milk was estimated to be 0.27% of the maternal weight-adjusted dose. In another study indomethacin levels were measured in breast milk of eight postpartum women using doses of 75 mg daily and the results were used to calculate an estimated infant daily dose. The estimated infant dose of indomethacin from breast milk was less than 30 mcg/day or 4.5 mcg/kg/day assuming breast milk intake of 150 mL/kg/day. This is 0.5% of the maternal weight-adjusted dosage or about 3% of the neonatal dose for treatment of patent ductus arteriosus.

8.3 Females and Males of Reproductive Potential

Infertility

Females

Based on the mechanism of action, the use of prostaglandin-mediated NSAIDs, including INDOCIN, may delay or prevent rupture of ovarian follicles, which has been associated with reversible infertility in some women. Published animal studies have shown that administration of prostaglandin synthesis inhibitors has the potential to disrupt prostaglandin-mediated follicular rupture required for ovulation. Small studies in women treated with NSAIDs have also shown a reversible delay in ovulation. Consider withdrawal of NSAIDs, including INDOCIN, in women who have difficulties conceiving or who are undergoing investigation of infertility.

8.4 Pediatric Use

Safety and effectiveness in pediatric patients 14 years of age and younger has not been established.

INDOCIN should not be prescribed for pediatric patients 14 years of age and younger unless toxicity or lack of efficacy associated with other drugs warrants the risk.

In experience with more than 900 pediatric patients reported in the literature or to the manufacturer who were treated with INDOCIN Capsules, side effects in pediatric patients were comparable to those reported in adults. Experience in pediatric patients has been confined to the use of INDOCIN Capsules.

If a decision is made to use indomethacin for pediatric patients two years of age or older, such patients should be monitored closely and periodic assessment of liver function is recommended. There have been cases of hepatotoxicity reported in pediatric patients with juvenile rheumatoid arthritis, including fatalities. If indomethacin treatment is instituted, a suggested starting dose is 1-2 mg/kg/day given in divided doses. Maximum daily dosage should not exceed 3 mg/kg/day or 150-200 mg/day, whichever is less. Limited data are available to support the use of a maximum daily dosage of 4 mg/kg/day or 150-200 mg/day, whichever is less. As symptoms subside, the total daily dosage should be reduced to the lowest level required to control symptoms, or the drug should be discontinued.

8.5 Geriatric Use

Elderly patients, compared to younger patients, are at greater risk for NSAID-associated serious cardiovascular, gastrointestinal, and/or renal adverse reactions. If the anticipated benefit for the elderly patient outweighs these potential risks, start dosing at the low end of the dosing range, and monitor patients for adverse effects [see Warnings and Precautions (5.1, 5.2, 5.3, 5.6, 5.14)].

Indomethacin may cause confusion or rarely, psychosis [see Adverse Reactions (6.1)]; physicians should remain alert to the possibility of such adverse effects in the elderly.

Indomethacin and its metabolites are known to be substantially excreted by the kidneys, and the risk of adverse reactions to this drug may be greater in patients with impaired renal function. Because elderly patients are more likely to have decreased renal function, use caution in this patient population, and it may be useful to monitor renal function [see Clinical Pharmacology (12.3)].

10 OVERDOSAGE

Symptoms following acute NSAID overdosages have been typically limited to lethargy, drowsiness, nausea, vomiting, and epigastric pain, which have been generally reversible with supportive care. Gastrointestinal bleeding has occurred. Hypertension, acute renal failure, respiratory depression, and coma have occurred, but were rare [see Warnings and Precautions (5.1, 5.2, 5.4, 5.6)].

Manage patients with symptomatic and supportive care following an NSAID overdosage. There are no specific antidotes. Consider emesis and/or activated charcoal (60 to 100 grams in adults, 1 to 2 grams per kg of body weight in pediatric patients) and/or osmotic cathartic in symptomatic patients seen within four hours of ingestion or in patients with a large overdosage (5 to 10 times the recommended dosage). Forced diuresis, alkalinization of urine, hemodialysis, or hemoperfusion may not be useful due to high protein binding.

For additional information about overdosage treatment contact a poison control center (1-800-222-1222).

11 DESCRIPTION

INDOCIN (indomethacin) Oral Suspension is a nonsteroidal anti-inflammatory drug, available as an oral suspension contain 25 mg of indomethacin per 5mL, alcohol 1%, and sorbic acid 0.1% added as a preservative for oral administration. The chemical name is -(4-chlorobenzoyl)-5-methoxy-2-methyl-1H-indole-3-acetic acid. The molecular weight is 357.8. Its molecular formula is C19H16ClNO4 , and it has the following chemical structure.

Indomethacin is a white to yellow crystalline powder. It is practically insoluble in water and sparingly soluble in alcohol. Indomethacin has a pKa of 4.5 and is stable in neutral or slightly acidic media and decomposes in strong alkali. The suspension has a pH of 4.0-5.0.

The inactive ingredients in INDOCIN include: antifoam AF emulsion, flavors, purified water, sodium hydroxide or hydrochloric acid to adjust pH, sorbitol solution, and tragacanth. INDOCIN Oral Suspension, 25 mg per 5 mL, is an off-white suspension with a pineapple coconut mint flavor.

12 CLINICAL PHARMACOLOGY

12.1 Mechanism of Action

Indomethacin has analgesic, anti-inflammatory, and antipyretic properties.

The mechanism of action of INDOCIN, like that of other NSAIDs, is not completely understood but involves inhibition of cyclooxygenase (COX-1 and COX-2).

Indomethacin is a potent inhibitor of prostaglandin synthesis in vitro. Indomethacin concentrations reached during therapy have produced in vivo effects. Prostaglandins sensitize afferent nerves and potentiate the action of bradykinin in inducing pain in animal models. Prostaglandins are mediators of inflammation. Because indomethacin is an inhibitor of prostaglandin synthesis, its mode of action may be due to a decrease of prostaglandins in peripheral tissues.

12.3 Pharmacokinetics

Absorption

Following single oral doses of INDOCIN Capsules 25 mg or 50 mg, indomethacin is readily absorbed, attaining peak plasma concentrations of about 1 and 2 mcg/mL, respectively, at about 2 hours. Orally administered INDOCIN Capsules are virtually 100% bioavailable, with 90% of the dose absorbed within 4 hours. A single 50 mg dose of INDOCIN Oral Suspension was found to be bioequivalent to a 50 mg INDOCIN Capsule when each was administered with food. With a typical therapeutic regimen of 25 or 50 mg three times a day, the steady-state plasma concentrations of indomethacin are an average 1.4 times those following the first dose.

Distribution

Indomethacin is highly bound to protein in plasma (about 99%) over the expected range of therapeutic plasma concentrations. Indomethacin has been found to cross the blood-brain barrier and the placenta, and appears in breast milk.

Elimination

Metabolism

Indomethacin exists in the plasma as the parent drug and its desmethyl, desbenzoyl, and desmethyldesbenzoyl metabolites, all in the unconjugated form. Appreciable formation of glucuronide conjugates of each metabolite and of indomethacin are formed.

Excretion

Indomethacin is eliminated via renal excretion, metabolism, and biliary excretion. Indomethacin undergoes appreciable enterohepatic circulation. About 60% of an oral dose is recovered in urine as drug and metabolites (26% as indomethacin and its glucuronide), and 33% is recovered in feces (1.5% as indomethacin). The mean half-life of indomethacin is estimated to be about 4.5 hours.

Specific Populations

Pediatric: The pharmacokinetics of INDOCIN has not been investigated in pediatric patients.

Race: Pharmacokinetic differences due to race have not been identified.

Hepatic Impairment: The pharmacokinetics of INDOCIN has not been investigated in patients with hepatic impairment.

Renal Impairment: The pharmacokinetics of INDOCIN has not been investigated in patients with renal impairment [see Warnings and Precautions (5.6)].

Drug Interaction Studies

Aspirin:

In a study in normal volunteers, it was found that chronic concurrent administration of 3.6 g of aspirin per day decreases indomethacin blood levels approximately 20% [see Drug Interactions (7)].

When NSAIDs were administered with aspirin, the protein binding of NSAIDs were reduced, although the clearance of free NSAID was not altered. The clinical significance of this interaction is not known. See Table 2 for clinically significant drug interactions of NSAIDs with aspirin [see Drug Interactions (7)].

Diflunisal:

In normal volunteers receiving indomethacin, the administration of diflunisal decreased the renal clearance and significantly increased the plasma levels of indomethacin [see Drug Interactions (7)].

13 NONCLINICAL TOXICOLOGY

13.1 Carcinogenesis, Mutagenesis, Impairment of Fertility

Carcinogenesis

In an 81-week chronic oral toxicity study in the rat at doses up to 1 mg/kg/day (0.05 times the MRHD on a mg/m^2 basis), indomethacin had no tumorigenic effect. Indomethacin produced no neoplastic or hyperplastic changes related to treatment in carcinogenic studies in the rat (dosing period 73 to 110 weeks) and the mouse (dosing period 62 to 88 weeks) at doses up to 1.5 mg/kg/day (0.04 times [mice] and 0.07 times [rats] the MRHD on a mg/m^2 basis, respectively).

Mutagenesis

Indomethacin did not have any mutagenic effect in in vitro bacterial tests and a series of in vivo tests including the host-mediated assay, sex-linked recessive lethals in Drosophila, and the micronucleus test in mice.

Impairment of Fertility

Indomethacin at dosage levels up to 0.5 mg/kg/day had no effect on fertility in mice in a two generation reproduction study (0.01 times the MRHD on a mg/m^2 basis) or a two litter reproduction study in rats (0.02 times the MRHD on a mg/m^2 basis).

14 CLINICAL STUDIES

INDOCIN has been shown to be an effective anti-inflammatory agent, appropriate for long-term use in rheumatoid arthritis, ankylosing spondylitis, and osteoarthritis.

INDOCIN affords relief of symptoms; it does not alter the progressive course of the underlying disease.

INDOCIN suppresses inflammation in rheumatoid arthritis as demonstrated by relief of pain, and reduction of fever, swelling and tenderness. Improvement in patients treated with INDOCIN for rheumatoid arthritis has been demonstrated by a reduction in joint swelling, average number of joints involved, and morning stiffness; by increased mobility as demonstrated by a decrease in walking time; and by improved functional capability as demonstrated by an increase in grip strength. INDOCIN may enable the reduction of steroid dosage in patients receiving steroids for the more severe forms of rheumatoid arthritis. In such instances the steroid dosage should be reduced slowly and the patients followed very closely for any possible adverse effects.

16 HOW SUPPLIED/STORAGE AND HANDLING

INDOCIN (indomethacin) Oral Suspension, 25 mg per 5 mL, is an off-white suspension with a pineapple coconut mint flavor. It is supplied as follows:

NDC 69344-101-01 in bottles of 237 mL

Storage

Store below 30°C (86°F). Avoid temperatures above 50°C (122°F). Do not freeze.

17 PATIENT COUNSELING INFORMATION

Advise the patient to read the FDA-approved patient labeling (Medication Guide) that accompanies each prescription dispensed. Inform patients, families, or their caregivers of the following information before initiating therapy with INDOCIN and periodically during the course of ongoing therapy.

Cardiovascular Thrombotic Events

Advise patients to be alert for the symptoms of cardiovascular thrombotic events, including chest pain, shortness of breath, weakness, or slurring of speech, and to report any of these symptoms to their health care provider immediately [see Warnings and Precautions (5.1)].

Gastrointestinal Bleeding, Ulceration, and Perforation

Advise patients to report symptoms of ulcerations and bleeding, including epigastric pain, dyspepsia, melena, and hematemesis to their health care provider. In the setting of concomitant use of low-dose aspirin for cardiac prophylaxis, inform patients of the increased risk for and the signs and symptoms of GI bleeding [see Warnings and Precautions (5.2)].

Hepatotoxicity

Inform patients of the warning signs and symptoms of hepatotoxicity (e.g., nausea, fatigue, lethargy, pruritus, diarrhea, jaundice, right upper quadrant tenderness, and “flu-like” symptoms). If these occur, instruct patients to stop INDOCIN and seek immediate medical therapy [see Warnings and Precautions (5.3)].

Heart Failure and Edema

Advise patients to be alert for the symptoms of congestive heart failure including shortness of breath, unexplained weight gain, or edema and to contact their healthcare provider if such symptoms occur [see Warnings and Precautions (5.5)].

Anaphylactic Reactions

Inform patients of the signs of an anaphylactic reaction (e.g., difficulty breathing, swelling of the face or throat). Instruct patients to seek immediate emergency help if these occur [see Contraindications (4) and Warnings and Precautions (5.7)].

Serious Skin Reactions, including DRESS

Advise patients to stop taking INDOCIN immediately if they develop any type of rash or fever and to contact their healthcare provider as soon as possible [see Warnings and Precautions (5.9. 5.10)].

Female Fertility

Advise females of reproductive potential who desire pregnancy that NSAIDs, including INDOCIN, may be associated with a reversible delay in ovulation [see Use in Specific Populations (8.3)].

Fetal Toxicity

Inform pregnant women to avoid use of INDOCIN and other NSAIDs starting at 30 weeks gestation because of the risk of the premature closing of the fetal ductus arteriosus. If
treatment with INDOCIN is needed for a pregnant woman between about 20 to 30 weeks gestation, advise her that she may need to be monitored for oligohydramnios, if treatment continues for longer than 48 hours [see Warnings and Precautions (5.11) and Use in Specific
Populations (8.1)].

Avoid Concomitant Use of NSAIDs

Inform patients that the concomitant use of INDOCIN with other NSAIDs or salicylates (e.g., diflunisal, salsalate) is not recommended due to the increased risk of gastrointestinal toxicity, and little or no increase in efficacy [see Warnings and Precautions (5.2) and Drug Interactions (7)]. Alert patients that NSAIDs may be present in “over the counter” medications for treatment of colds, fever, or insomnia.

Use of NSAIDs and Low-Dose Aspirin

Inform patients not to use low-dose aspirin concomitantly with INDOCIN until they talk to their healthcare provider [see Drug Interactions (7)].

Manufactured by:
Patheon Inc.
Whitby, Ontario L1N 5Z5, Canada

Distributed by:
Zyla Life Sciences US Inc., Wayne, PA 19087

©2024 Zyla Life Sciences US Inc. All rights reserved.

LBL# 801.03

Medication Guide for Nonsteroidal Anti-inflammatory Drugs (NSAIDs)

What is the most important information I should know about medicines called Nonsteroidal Anti-inflammatory Drugs (NSAIDs)?

NSAIDs can cause serious side effects, including:

- Increased risk of a heart attack or stroke that can lead to death. This risk may happen early in treatment and may increase:
  - with increasing doses of NSAIDs
  - with longer use of NSAIDs
  Do not take NSAIDs right before or after a heart surgery called a “coronary artery bypass graft (CABG)."
  Avoid taking NSAIDs after a recent heart attack, unless your healthcare provider tells you to. You may have an increased risk of another heart attack if you take NSAIDs after a recent heart attack.
- Increased risk of bleeding, ulcers, and tears (perforation) of the esophagus (tube leading from the mouth to the stomach), stomach and intestines:
  - anytime during use
  - without warning symptoms
  - that may cause death
  The risk of getting an ulcer or bleeding increases with:
  - past history of stomach ulcers, or stomach or intestinal bleeding with use of NSAIDs
  - taking medicines called “corticosteroids”, “anticoagulants”, “SSRIs”, or “SNRIs”
  - increasing doses of NSAIDs
  - longer use of NSAIDs
  - smoking
  - drinking alcohol
  - older age
  - poor health
  - advanced liver disease
  - bleeding problems
  NSAIDs should only be used:
  - exactly as prescribed
  - at the lowest dose possible for your treatment
  - for the shortest time needed

What are NSAIDs?
NSAIDs are used to treat pain and redness, swelling, and heat (inflammation) from medical conditions such as different types of arthritis, menstrual cramps, and other types of short-term pain.

Who should not take NSAIDs?
Do not take NSAIDs:

- if you have had an asthma attack, hives, or other allergic reaction with aspirin or any other NSAIDs.
- right before or after heart bypass surgery.

Before taking NSAIDs, tell your healthcare provider about all of your medical conditions, including if you:

- have liver or kidney problems
- have high blood pressure
- have asthma
- are pregnant or plan to become pregnant. Taking NSAIDs at about 20 weeks of pregnancy or later may
  harm your unborn baby. If you need to NSAIDs for more than 2 days when you are between 20 and 30
  weeks of pregnancy, your healthcare provider may need to monitor the amount of fluid in your womb
  around your baby. You should not take NSAIDs after about 30 weeks of pregnancy.
- are breastfeeding or plan to breast feed.

Tell your healthcare provider about all of the medicines you take, including prescription or over-the- counter medicines, vitamins or herbal supplements. NSAIDs and some other medicines can interact with each other and cause serious side effects. Do not start taking any new medicine without talking to your healthcare provider first.

What are the possible side effects of NSAIDs?
NSAIDs can cause serious side effects, including:

See “What is the most important information I should know about medicines called Nonsteroidal Anti- inflammatory Drugs (NSAIDs)?”

- new or worse high blood pressure
- heart failure
- liver problems including liver failure
- kidney problems including kidney failure
- low red blood cells (anemia)
- life-threatening skin reactions
- life-threatening allergic reactions
- Other side effects of NSAIDs include: stomach pain, constipation, diarrhea, gas, heartburn, nausea, vomiting, and dizziness.

Get emergency help right away if you get any of the following symptoms:

- shortness of breath or trouble breathing
- chest pain
- weakness in one part or side of your body
- slurred speech
- swelling of the face or throat

Stop taking your NSAID and call your healthcare provider right away if you get any of the following symptoms:

- nausea
- more tired or weaker than usual
- diarrhea
- itching
- your skin or eyes look yellow
- indigestion or stomach pain
- flu-like symptoms
- vomit blood
- there is blood in your bowel movement or it is black and sticky like tar
- unusual weight gain
- skin rash or blisters with fever
- swelling of the arms, legs, hands and feet

If you take too much of your NSAID, call your healthcare provider or get medical help right away.
These are not all the possible side effects of NSAIDs. For more information, ask your healthcare provider or pharmacist about NSAIDs.

Call your doctor for medical advice about side effects. You may report side effects to FDA at 1-800-FDA-1088.

Other information about NSAIDs

- Aspirin is an NSAID but it does not increase the chance of a heart attack. Aspirin can cause bleeding in the brain, stomach, and intestines. Aspirin can also cause ulcers in the stomach and intestines.
- Some NSAIDs are sold in lower doses without a prescription (over-the-counter). Talk to your healthcare provider before using over-the-counter NSAIDs for more than 10 days.

General information about the safe and effective use of NSAIDs
Medicines are sometimes prescribed for purposes other than those listed in a Medication Guide. Do not use NSAIDs for a condition for which it was not prescribed. Do not give NSAIDs to other people, even if they have the same symptoms that you have. It may harm them.

If you would like more information about NSAIDs, talk with your healthcare provider. You can ask your pharmacist or healthcare provider for information about NSAIDs that is written for health professionals.

Manufactured by:
Patheon Inc.111 Consumers Dr.
Whitby ON L1N 5Z5 Canada
Distributed by:
Zyla Life Sciences US Inc., Wayne, PA 19087
For more information, go to www.zyla com or call 1-800-518-1084

This Medication Guide has been approved by the U.S. Food and Drug Administration.

Revised: 04/2021